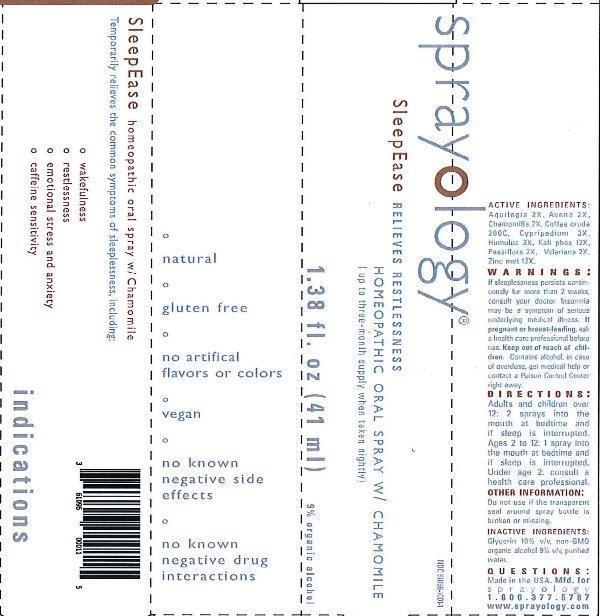 DRUG LABEL: Sprayology SleepEase
NDC: 61096-1001 | Form: LIQUID
Manufacturer: Eight and Company
Category: homeopathic | Type: HUMAN OTC DRUG LABEL
Date: 20160728

ACTIVE INGREDIENTS: AQUILEGIA VULGARIS 2 [hp_X]/41 mL; AVENA SATIVA FLOWERING TOP 2 [hp_X]/41 mL; MATRICARIA RECUTITA 2 [hp_X]/41 mL; ARABICA COFFEE BEAN 200 [hp_C]/41 mL; CYPRIPEDIUM PARVIFOLUM ROOT 3 [hp_X]/41 mL; HOPS 3 [hp_X]/41 mL; POTASSIUM PHOSPHATE, DIBASIC 12 [hp_X]/41 mL; PASSIFLORA INCARNATA FLOWERING TOP 2 [hp_X]/41 mL; VALERIAN 2 [hp_X]/41 mL; ZINC 12 [hp_X]/41 mL
INACTIVE INGREDIENTS: GLYCERIN; ALCOHOL; WATER

Sprayology SleepEase

Active Ingredient: Aquilegia vulgaris 2X, Avena sativa 2X, Chamomilla 2X, Coffea cruda 200C, Cypripedium pubescens 3X, Humulus lupulus 3X, Kali phosphoricum 12X, Passiflora incarnata 2X, Valeriana officinalis 2X, Zincum metallicum 12X.

WARNINGS

Warnings: If sleeplessness persists continuously for more than 2 weeks, consult your doctor. Insomnia may be a symptom of serious underlying medical illness. If pregnant or breast-feeding, ask a health care professional before use. Keep out of reach of children. Contains alcohol, in case of overdose, get medical help or contact a Poison Control Center right away.

Keep out of reach of children.

INDICATIONS AND USAGE

Temporarily relieves the common symptoms of sleeplessness, including:

- wakefulness
- restlessness
- emotional stress and anxiety
- caffeine sensitivity

Directions:

- Adults and children over 12: 2 sprays into the mouth at bedtime and if sleep is interrupted.
- Ages 2 to 12: 1 spray into the mouth at bedtime and if sleep is interrupted.
- Under age 2: consult a health care professional.

Other Information: Do not use if the transparent seal around spray bottle is broken or missing.

INACTIVE INGREDIENT

Inactive Ingredients: Glycerin 10%, v/v, non-GMO organic alcohol 9% v/v and purified water.

PURPOSE

Temporarily relieves the common symptoms of sleeplessness, including:

° wakefulness

° restlessness

° emotional stress and anxiety

° caffeine sensitivity

° natural

° gluten free

° no artifical flavors or colors

° vegan

° no known negative side effects

° no known negative drug interactions